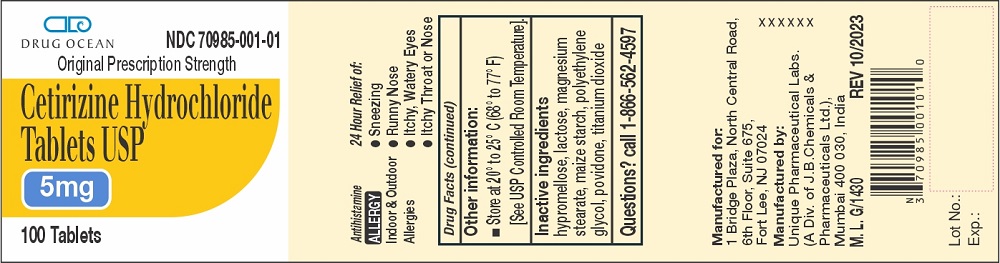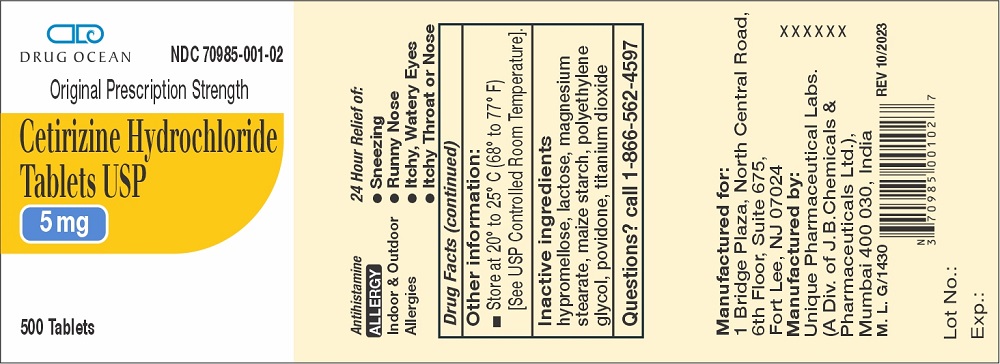 DRUG LABEL: Cetirizine Hydrochloride
NDC: 70985-001 | Form: TABLET
Manufacturer: Drug Ocean LLC
Category: otc | Type: HUMAN OTC DRUG LABEL
Date: 20231223

ACTIVE INGREDIENTS: CETIRIZINE HYDROCHLORIDE 5 mg/1 1
INACTIVE INGREDIENTS: HYPROMELLOSES; LACTOSE; MAGNESIUM STEARATE; STARCH, CORN; POLYETHYLENE GLYCOL, UNSPECIFIED; POVIDONE; TITANIUM DIOXIDE

Cetirizine Hydrochloride Tablets USP , 5 mg
Drug Facts

Active Ingredients

Active Ingredient (in each tablet) Purpose
Cetirizine HCl USP 5 mg.....................................................................................Antihistimine

Uses

INDICATIONS AND USAGE

Temporarily relieves these symptoms due to hay fever or other upper respiratory allergies:

- runny nose
- sneezing
- itchy, watery eyes
- itching of the nose or throat

Warnings

Do Not Use if you have ever had an allergic reaction to this product or any of its ingredients or to an antihistamine containing hydroxyzine.

Ask a doctor before use if you have liver or kidney disease. Your doctor should determine if you need a different dose.

Ask a doctor or pharmacist before use if you are taking tranquilizers or sedatives.

When using this product

- drowsines may occur
- avoid alcoholic drinks
- alcohol, sedatives, and tranquilizers may increase drowsiness
- be careful when driving a motor vehicle or operating machinary.

Stop use and ask a doctor if an allergic reaction to this product occurs. Seek medical help right away.

If pregnant or breast-feeding:

- if breast-feeding: not recommended
- if pregnant: ask a health professional before use.

Keep out of reach of children.

In case of overdose, get medical help or contact Poison Control Center right away. (1-800-222-1222)

Directions

Adults and children 6 years and over | 1 to 2 tablets once daily depending upon severity of symptoms; do not take more than 2 tablets in 24 hours.
Adults 65 years and over | 1 tablet1 tablet once a day; do not take more than 1 tablet in 24 hours.
Children under 6 years of age | Ask a doctor
Consumers with liver or kidney disease | Ask a doctor

Other Information

Store between 20° to 25°C (68° to 77°F) [See USP Controlled Room Temperature.]

Inactive Ingredients

hypromellose, lactose, magnesium stearate, maize starch, polyethylene glycol, povidone, titanium dioxide.

Questions?

Call 1-866-562-4597

Manufactured for:

Drug Ocean, LLC
1 Bridge Plaza, North Central Road,

6th Floor, Suite 675,

Fort Lee, NJ 07024

Manufactured by:

Unique Pharmaceutical Laboratories
(A Div. of J. B. Chemicals &Pharmaceuticals Ltd.),
Mumbai 400 030, India

M.L. G/1430

Rev. 12/2023

Cetirizine Hydrochloride Tablets 5 mg Container Label

DRUG OCEAN NDC 70985-001-01

Original Prescription Strength

Cetirizine Hydrochloride
Tablets USP

5 mg

100 Tablets

DRUG OCEAN NDC 70985-001-02

Original Prescription Strength

Cetirizine Hydrochloride
Tablets USP

5 mg

500 Tablets